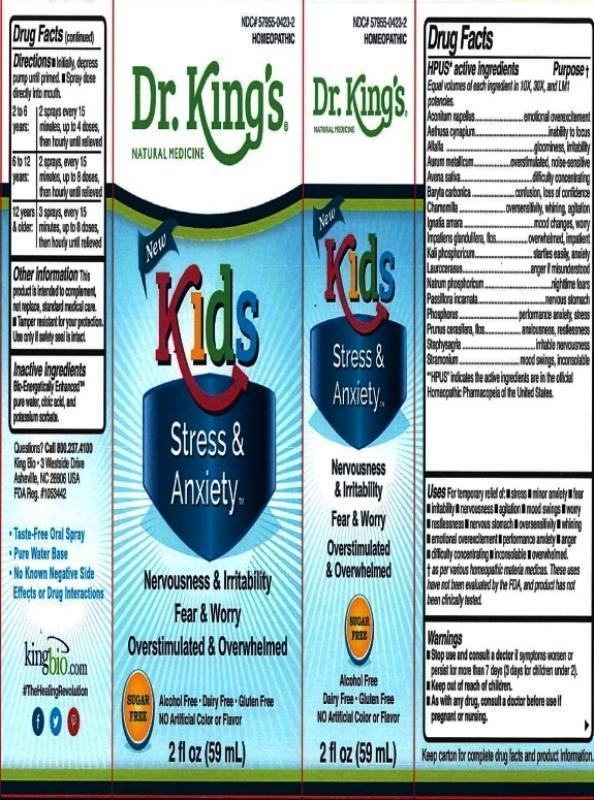 DRUG LABEL: Kids Stress and Anxiety
NDC: 57955-0423 | Form: LIQUID
Manufacturer: King Bio Inc.
Category: homeopathic | Type: HUMAN OTC DRUG LABEL
Date: 20160901

ACTIVE INGREDIENTS: ACONITUM NAPELLUS 10 [hp_X]/59 mL; AETHUSA CYNAPIUM 10 [hp_X]/59 mL; ALFALFA 10 [hp_X]/59 mL; GOLD 10 [hp_X]/59 mL; AVENA SATIVA FLOWERING TOP 10 [hp_X]/59 mL; BARIUM CARBONATE 10 [hp_X]/59 mL; MATRICARIA RECUTITA 10 [hp_X]/59 mL; STRYCHNOS IGNATII SEED 10 [hp_X]/59 mL; IMPATIENS GLANDULIFERA FLOWER 10 [hp_X]/59 mL; POTASSIUM PHOSPHATE, DIBASIC 10 [hp_X]/59 mL; PRUNUS LAUROCERASUS LEAF 10 [hp_X]/59 mL; SODIUM PHOSPHATE, DIBASIC, HEPTAHYDRATE 10 [hp_X]/59 mL; PASSIFLORA INCARNATA FLOWERING TOP 10 [hp_X]/59 mL; PHOSPHORUS 10 [hp_X]/59 mL; PRUNUS CERASIFERA FLOWER 10 [hp_X]/59 mL; DELPHINIUM STAPHISAGRIA SEED 10 [hp_X]/59 mL; DATURA STRAMONIUM 10 [hp_X]/59 mL
INACTIVE INGREDIENTS: ANHYDROUS CITRIC ACID; POTASSIUM SORBATE; WATER

Kids Stress and Anxiety™

ACTIVE INGREDIENT

Drug Facts__________________________________________________________________________________________________________

HPUS active ingredients: Aconitum napellus, Aethusa cynapium, Alfalfa, Aurum metallicum, Avena sativa, Baryta carbonica, Chamomilla, Ignatia amara, Impatiens glandulifera, flos, Kali phosphoricum, Laurocerasus, Natrum phosphoricum, Passiflora incarnata, Phosphorus, Prunus cerasifera, flos, Staphysagria, Stramonium. Equal volumes of each ingredient in 10X, 30X, LM1 potencies.

INDICATIONS AND USAGE

Uses for temporary relief of symptoms:

- stress
- minor anxiety
- fear
- irritability
- nervousness
- agitation
- mood swings
- worry
- restlessness
- nervous stomach
- oversensitivity
- whining
- emotional overexcitement
- performance anxiety
- anger
- difficulty concentrating
- inconsolable
- overwhelmed

† as per various homeopathic materia medicas. These uses have not been evaluated by the FDA, and product has not been clinically tested.

Warnings

- Stop use and consult a doctor if symptoms worsen or persist for more than 7 days (3 days for children under 2).
- Keep out of reach of children.
- As with any drug, consult a doctor before use if pregnant or nursing.

- Keep out of reach of children.

Directions

- Initially, depress pump until primed.
- Spray one dose directly into mouth.
- 2 to 6 years: 2 sprays every 15 minutes, up to 4 doses, then hourly until relieved.
- 6 to 12 Years: 2 sprays, every 15 minutes, up to 8 doses, then hourly until relieved.
- 12 years & older: 3 sprays, every 15 minutes, up to 8 doses, then hourly until relieved.

Other information

This product is intended to complement, not replace, standard medical care. • Tamper resistant for your protection. Use only if safety seal is intact.

Inactive Ingredients:

Bio-Energetically Enhanced™ pure water, citric acid and potassium sorbate.

PURPOSE

Drug Facts_________________________________________________________________________________________________

HPUS* active ingredients Purpose†

Equal volumes of each ingredient in 10X, 30X, and LM1 potencies.

Aconitum napellus........................................emotional overexcitement

Aethusa cynapium.....................................................inability to focus

Alfalfa..............................................................gloominess, irritability

Aurum metallicum.................................overstimulated, noise-sensitive

Avena sativa....................................................difficulty concentrating

Baryta carbonica........................................confusion, loss of confidence

Chamomilla.......................................oversensitivity, whining, agitation

Ignatia amara....................................................mood changes, worry

Impatiens glandulifera, flos.............................overwhelmed, impatient

Kali phosphoricum.............................................startles easily, anxiety

Laurocerasus...................................................anger if misunderstood

Natrum phosphoricum.................................................nighttime fears

Passiflora incarnata..................................................nervous stomach

Phosphorus..............................................performance anxiety, stress

Prunus cerasifera, flos..................................anxiousness, restlessness

Staphysagria.....................................................irritable nervousness

Stramonium..............................................mood swings, inconsolable

*"HPUS" indicates the active ingredients are in the official Homeopathic Pharmacopeia of the United States.